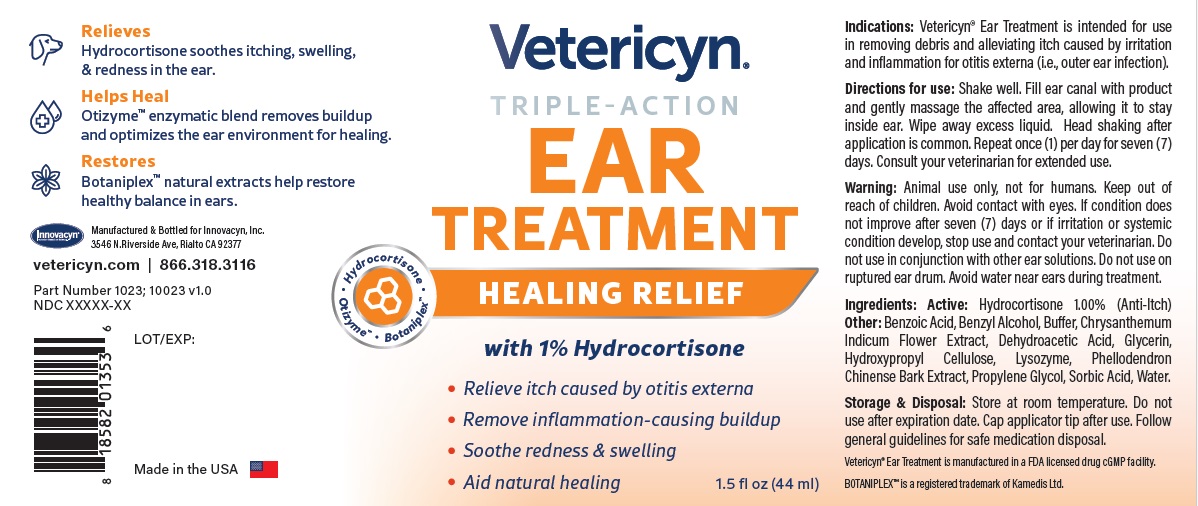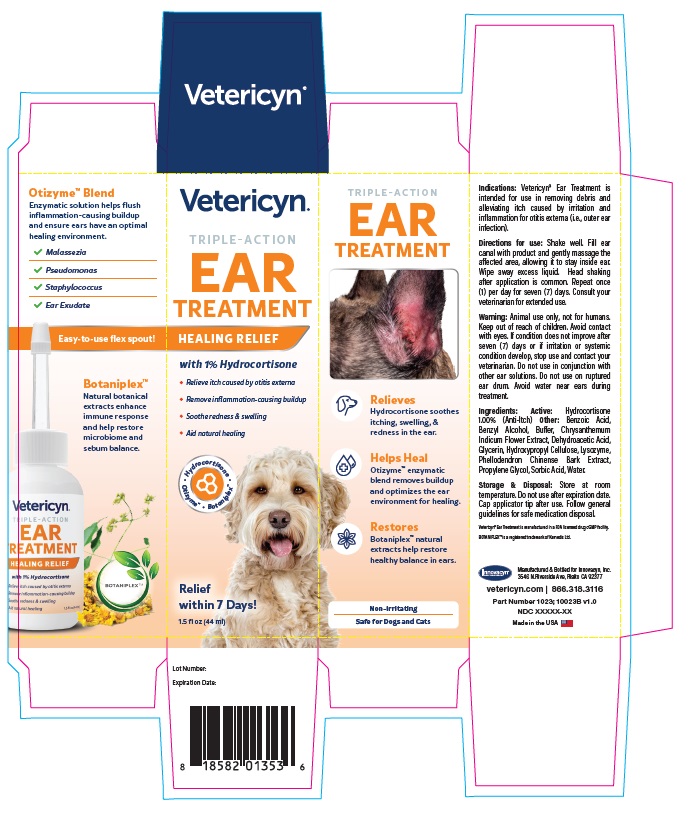 DRUG LABEL: Vetericyn Triple Action Ear Treatment
NDC: 70489-1023 | Form: LIQUID
Manufacturer: INNOVACYN INC.
Category: animal | Type: OTC ANIMAL DRUG LABEL
Date: 20251125

ACTIVE INGREDIENTS: HYDROCORTISONE 1 g/100 mL
INACTIVE INGREDIENTS: PROPYLENE GLYCOL; GLYCERIN; BENZYL ALCOHOL; BENZOIC ACID; SORBIC ACID; DEHYDROACETIC ACID; CHRYSANTHEMUM INDICUM FLOWER; HYDROXYPROPYL CELLULOSE, UNSPECIFIED; WATER; LYSOZYME; SODIUM HYDROXIDE; PHELLODENDRON CHINENSE WHOLE

Active Ingredient

Hydrocortisone

Description

Vetericyn® Ear Treatment is intended for use in removing debris and alleviating itch caused by irritation and inflammation for otitis externa (i.e., outer ear infection).

Dosage/Administration

Shake well. Fill ear canal with product and gently massage the affected area, allowing it to stay inside ear. Wipe away excess liquid. Head shaking after application is common. Repeat once (1) per day for seven (7)days. Consult your veterinarian for extended use.

Warning

Animal use only, not for humans. Keep out of reach of children. Avoid contact with eyes. If condition does not improve after seven (7) days or if irritation or systemic condition develop, stop use and contact your veterinarian. Do not use in conjunction with other ear solutions. Do not use on ruptured ear drum. Avoid water near ears during treatment.

Inactive Ingredient

Benzoic Acid, Benzyl Alcohol, Buffer, Chrysanthemum Indicum Flower Extract, Dehydroacetic Acid, Glycerin,Hydroxypropyl Cellulose, Lysozyme, Phellodendron Chinense Bark Extract, Propylene Glycol, Sorbic Acid, Water.

Precautions

Store at room temperature. Do not use after expiration date. Cap applicator tip after use. Follow general guidelines for safe medication disposal.

Questions

vetericyn.com | 866.318.3116